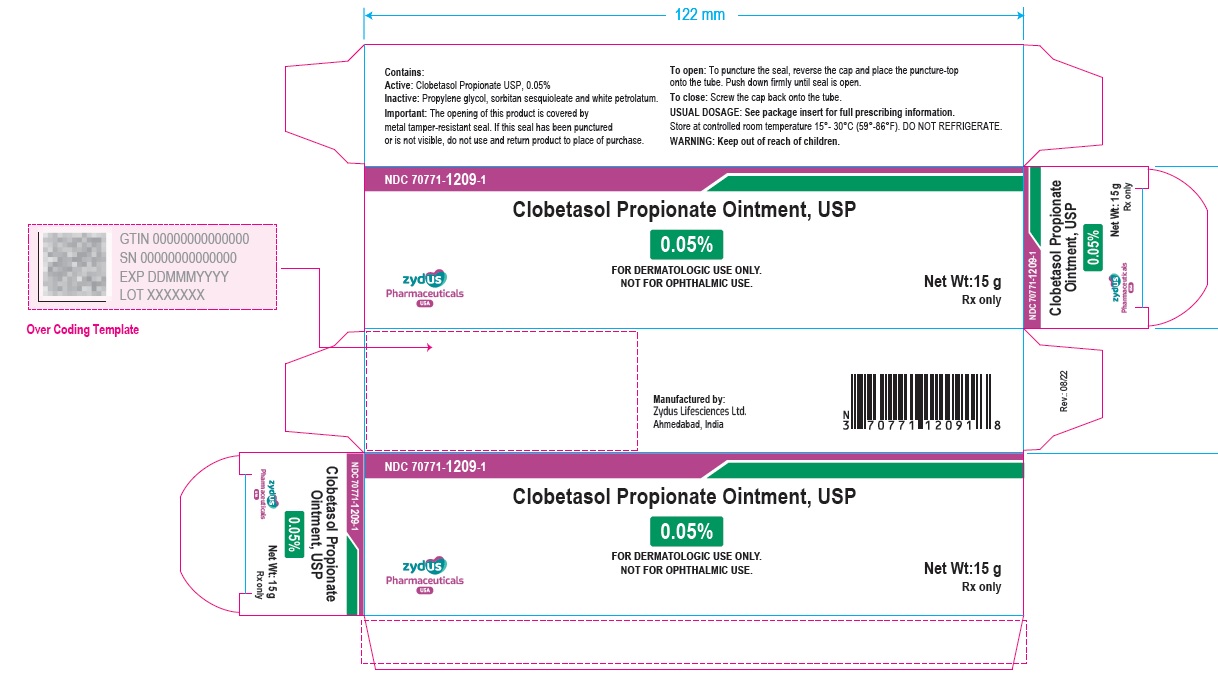 DRUG LABEL: CLOBETASOL PROPIONATE
NDC: 70771-1209 | Form: OINTMENT
Manufacturer: Zydus Lifesciences Limited
Category: prescription | Type: HUMAN PRESCRIPTION DRUG LABEL
Date: 20241126

ACTIVE INGREDIENTS: CLOBETASOL PROPIONATE 0.5 mg/1 g
INACTIVE INGREDIENTS: PROPYLENE GLYCOL; SORBITAN SESQUIOLEATE; PETROLATUM

CLOBETASOL PROPIONATE OINTMENT USP, 0.05%

PACKAGE LABEL.PRINCIPAL DISPLAY PANEL

NDC 70771-1209-1

Clobetasol Propionate Ointment USP, 0.05%

Rx only

15 g